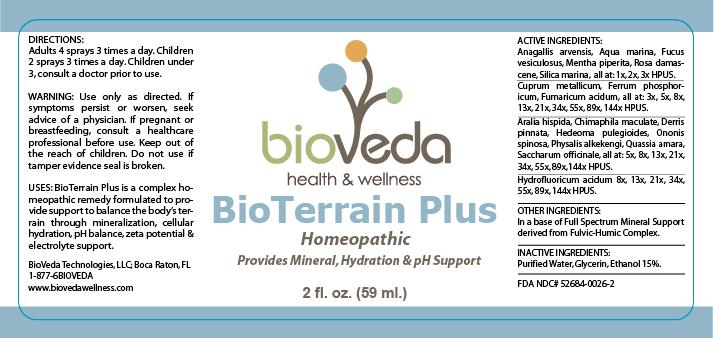 DRUG LABEL: BioTerrain Plus
NDC: 52684-0026 | Form: SPRAY
Manufacturer: BioVeda
Category: homeopathic | Type: HUMAN OTC DRUG LABEL
Date: 20120603

ACTIVE INGREDIENTS: ANAGALLIS ARVENSIS 3 [hp_X]/59 mL; Water 3 [hp_X]/59 mL; MENTHA PIPERITA 3 [hp_X]/59 mL; ROSA DAMASCENA FLOWERING TOP 3 [hp_X]/59 mL; SILICON DIOXIDE 3 [hp_X]/59 mL; Fucus Vesiculosus 3 [hp_X]/59 mL; COPPER 144 [hp_X]/59 mL; FERROSOFERRIC PHOSPHATE 144 [hp_X]/59 mL; ARALIA HISPIDA ROOT 144 [hp_X]/59 mL; CHIMAPHILA MACULATA 144 [hp_X]/59 mL; DALBERGIA PINNATA ROOT 144 [hp_X]/59 mL; HEDEOMA PULEGIOIDES 1 [hp_X]/59 mL; ONONIS CAMPESTRIS 144 [hp_X]/59 mL; QUASSIA AMARA WOOD 144 [hp_X]/59 mL; SUCROSE 144 [hp_X]/59 mL; HYDROFLUORIC ACID 144 [hp_X]/59 mL
INACTIVE INGREDIENTS: Water; ALCOHOL; GLYCERIN; FULVIC ACID

BioTerrain Plus

ACTIVE INGREDIENTS:

Anagallis arvensis, Aqua marina, Fucus vesiculosus, Mentha piperita, Rosa damascene; Silica marina 1x 2x 3x HPUS

Cuprum metallicum: Ferrum phosphoricum; Fumaricum acidum; All at: 3x 5x 8x 13x 21x 34x 55x 89x 144x HPUS

Aralia hispida; Chimaphila maculate; Derris pinnata; Hedeoma pulegioides; Ononis spinosa, Physalis alkekengi, Quassia amara; Saccharum officinale All at: 5x 8x 13x 21x 34x 55x 89x 144x HPUS

Hydrofluoricum acidum 8x 13x 21x 34x 55x 89x 144x HPUS

USES:

BioTerrain Plus is a complex homeopathic remedy formulated to provide support to balance the body's terrain through mineralization, cellular hydration, pH balance, zeta potential and electrolyte support.

WARNING:

Use only as directed.

ASK DOCTOR

If symptoms persist or worsen, seek advice of a physician.

PREGNANCY OR BREAST FEEDING

If pregnant or breastfeeding, consult a healthcare professional before use.

Keep out of the reach of children.

Do not use if tamper evidence seal is broken.

DIRECTIONS:

Adults 4 sprays 3 times a day.

Children 2 sprays 3 times a day.

Children under 3, consult a doctor prior to use.

Other Ingredients:

In a base of Full Spectrum Mineral Support derived from Fluvic-Humic Complex.

INACTIVE INGREDIENTS:

Purified Water, Glycerin, Ethanol 15%

QUESTIONS:

BioVeda Technologies, LLC

Boca Raton, FL

1-877-6BIOVEDA

www.biovedawellness.com

PRINCIPAL DISPLAY PANEL

BioTerrain Plus

Homeopathic

Provides Mineral, Hydration and pH Support.